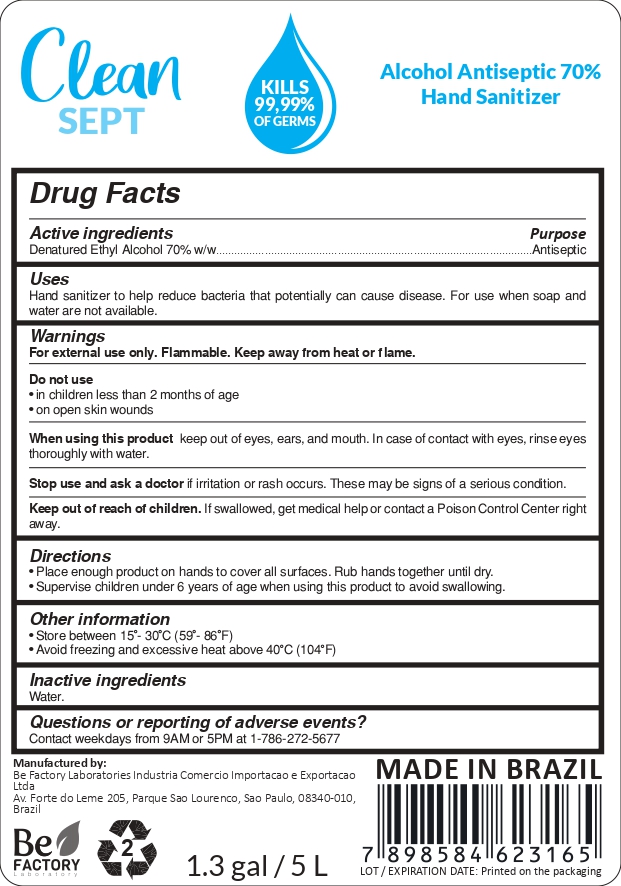 DRUG LABEL: Clean Sept Alcohol Antiseptic 70% Hand Sanitizer
NDC: 79916-002 | Form: LIQUID
Manufacturer: BE FACTORY LABORATORIES INDUSTRIA COMERCIO IMPORTACAO E EXPORTACAO LTDA
Category: otc | Type: HUMAN OTC DRUG LABEL
Date: 20201207

ACTIVE INGREDIENTS: ALCOHOL 70 mL/100 mL
INACTIVE INGREDIENTS: WATER 30 mL/100 mL

NO CHANGES NOTIFICATION

Drug Facts Panel - Active Ingredients

Denatured Ethyl Alcohol 70% w/w. Purpose: Antiseptic.

Drug Facts Panel - Purpose

Purpose: Antiseptic

Drug Facts Panel - Use

Use: Hand sanitizer to help reduce bacteria that potentially can cause disease. For use when soap and water are not available.

Drug Facts Panel - Warnings

For external use only. Flammable. Keep away from heat or flame.
Do not use
● in children less than 2 months of age
● on open skin wounds
When using this product keep out of eyes, ears, and mouth. In case of contact with eyes, rinse eyes thoroughly with water.
Stop use and ask a doctor if irritation or rash occurs. These may be signs of a serious condition.
Keep out of reach of children. If swallowed, get medical help or contact a Poison Control Center right away.

Do not use
● in children less than 2 months of age
● on open skin wounds

When using this product keep out of eyes, ears, and mouth. In case of contact with eyes, rinse eyes thoroughly with water.

Stop use and ask a doctor if irritation or rash occurs. These may be signs of a serious condition.

Keep out of reach of children. If swallowed, get medical help or contact a Poison Control Center right away.

Drug Facts Panel - Directions

Place enough product on hands to cover all surfaces. Rub hands together until dry.
Supervise children under 6 years of age when using this product to avoid swallowing.

Drug Facts Panel - Other Information

Store between 15-30 °C (59-86 °F)
Avoid freezing and excessive heat above 40 °C (104 °F)

Drug Facts Panel - Inactive Ingredients

Water.

Package Label - Principal Display Panel

5000 ml, NDC 79916-002-01